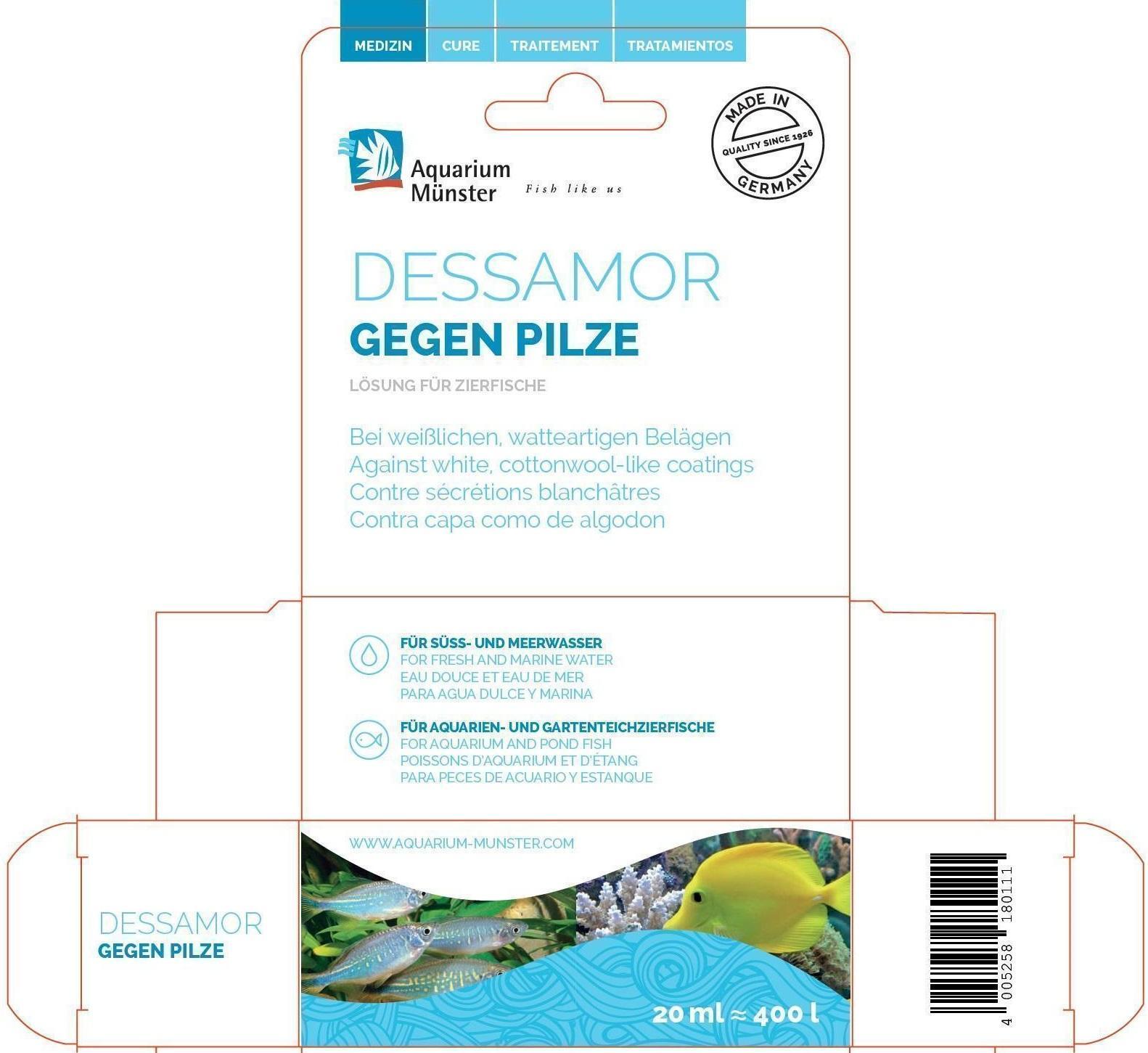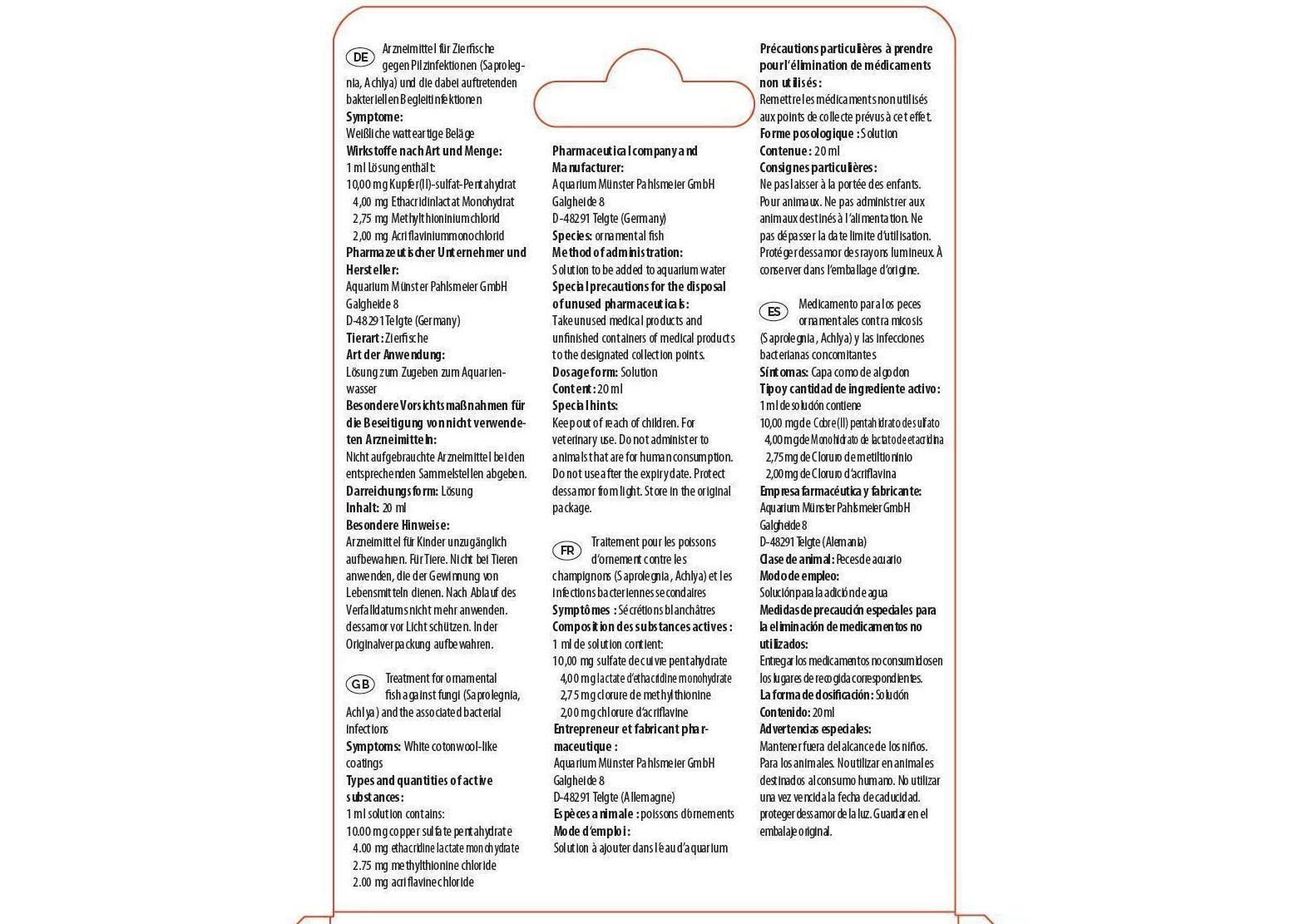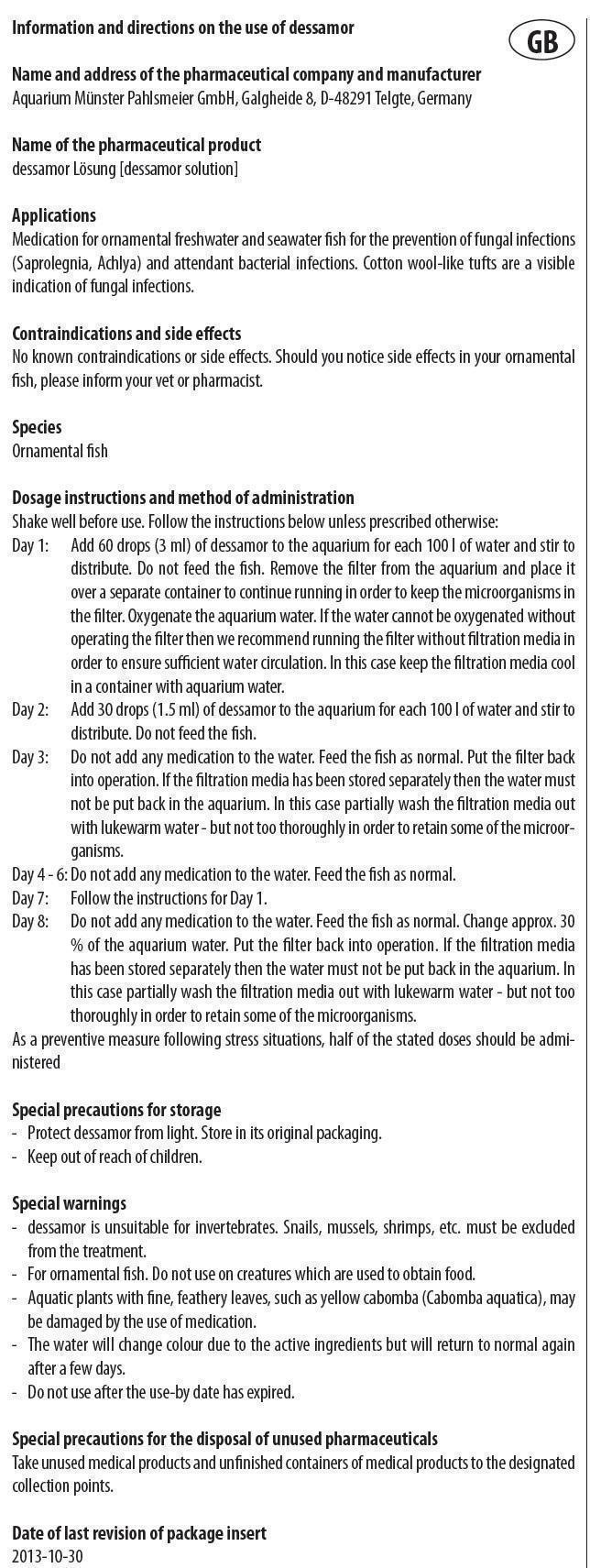 DRUG LABEL: DESSAMOR
NDC: 86052-003 | Form: SOLUTION
Manufacturer: Aquarium Muenster Pahlsmeier GmbH
Category: animal | Type: OTC ANIMAL DRUG LABEL
Date: 20240419

ACTIVE INGREDIENTS: CUPRIC SULFATE 10 mg/1 mL; ETHACRIDINE LACTATE 4 mg/1 mL; METHYLENE BLUE ANHYDROUS 2.75 mg/1 mL; ACRIFLAVINE HYDROCHLORIDE 2 mg/1 mL

DESSAMOR

Information and directions on the use of dessamor

Name and address of the pharmaceutical company and manufacturer
Aquarium Münster Pahlsmeier GmbH, Galgheide 8, D-48291 Telgte, Germany

Name of the pharmaceutical product
dessamor Losung [dessamor solution]

Applications

Medication for ornamental freshwater and seawater fish for the prevention of fungal infections (Saprolegnia, Achlya) and attendant bacterial infections. Cotton wool-like tufts are a visible indication of fungal infections.

Types and quantities of active substances:

1 ml solution contains:

10.00 mg copper sulfate pentahydrate

4.00 mg ethacridine lactate monohydrate

2.75 mg methylthionine chloride

2.00 mg acriflavine chloride

Contraindications and side effects

No known contraindications or side effects. Should you notice side effects in your ornamental fish, please inform your vet or pharmacist.

Species

Ornamental fish

Dosage instructions and method of administration

Shake well before use. Follow the instructions below unless prescribed otherwise:
Day 1: Add 60 drops (3 ml) of dessamor to the aquarium for each 100 l of water and stir to distribute. Do not feed the fish. Remove the filter from the aquarium and place it over a separate container to continue running in order to keep the microorganisms in the filter. Oxygenate the aquarium water. If the water cannot be oxygenated without operating the filter then we recommend running the filter without filtration media in order to ensure sufficient water circulation. In this case keep the filtration media coolin a container with aquarium water.
Day 2: Add 30 drops (1.5 ml) of dessamor to the aquarium for each 100 l of water and stir to distribute. Do not feed the fish.
Day 3: Do not add any medication to the water. Feed the fish as normal. Put the filter back into operation. If the filtration media has been stored separately then the water must not be put back in the aquarium. In this case partially wash the filtration media out with lukewarm water - but not too thoroughly in order to retain some of the microorganisms.
Day 4 - 6: Do not add any medication to the water. Feed the fish as normal.
Day 7: Follow the instructions for Day 1.

Day 8: Do not add any medication to the water. Feed the fish as normal. Change approx. 30% of the aquarium water. Put the filter back into operation. If the filtration media has been stored separately then the water must not be put back in the aquarium. Inthis case partially wash the filtration media out with lukewarm water - but not too thoroughly in order to retain some of the microorganisms.
As a preventive measure following stress situations, half of the stated doses should be administered

Special precautions for storage

- Protect dessamor from light. Store in its original packaging.

- Keep out of reach of children.

Special warnings

- dessamor is unsuitable for invertebrates. Snails, mussels, shrimps, etc. must be excluded from the treatment.
- For ornamental fish. Do not use on creatures which are used to obtain food.
- Aquatic plants with fine, feathery leaves, such as yellow cabomba (Cabomba aquatica), may be damaged by the use of medication.
- The water will change colour due to the active ingredients but will return to normal again after a few days.
- Do not use after the use-by date has expired.

Special precautions for the disposal of unused pharmaceuticals

Take unused medical products and unfinished containers of medical products to the designated collection points.

Date of last revision of package insert
2013-10-30